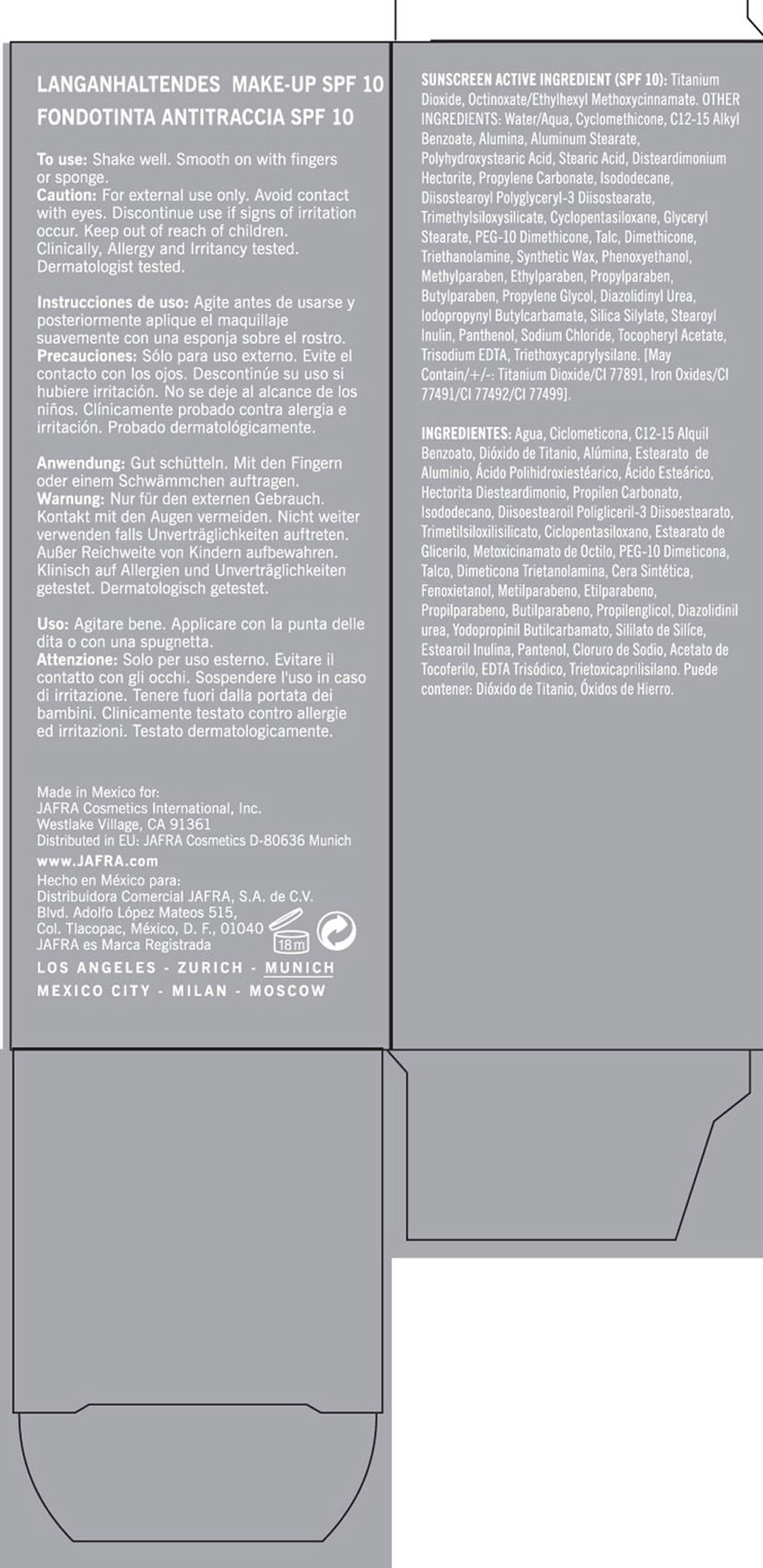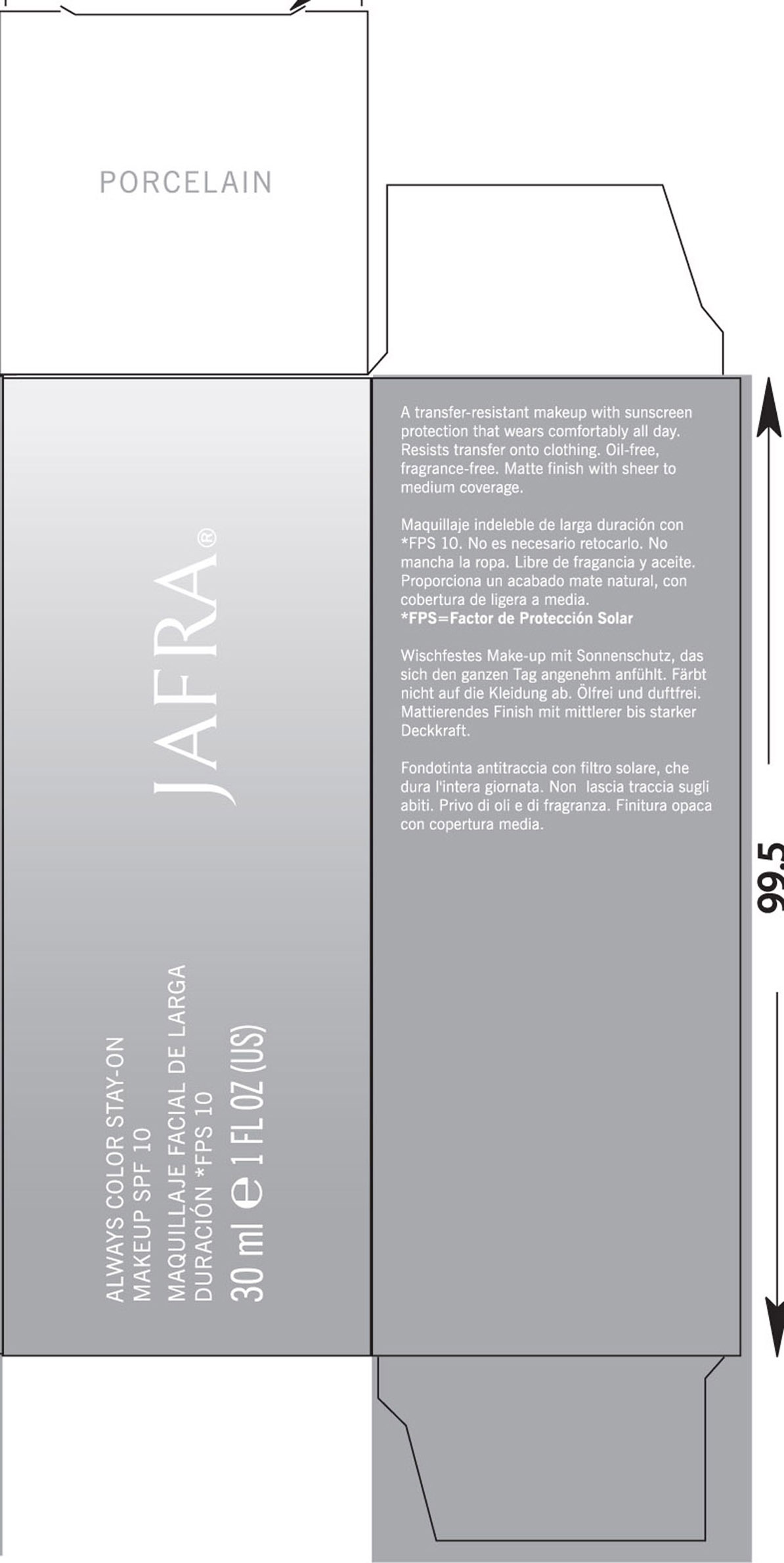 DRUG LABEL: Bisque
NDC: 68828-075 | Form: LOTION
Manufacturer: Jafra Cosmetics International Inc
Category: otc | Type: HUMAN OTC DRUG LABEL
Date: 20120608

ACTIVE INGREDIENTS: TITANIUM DIOXIDE 8 mL/100 mL; OCTINOXATE 2.5 mL/100 mL
INACTIVE INGREDIENTS: WATER ; CYCLOMETHICONE; ALKYL (C12-15) BENZOATE; ALUMINUM OXIDE; ALUMINUM STEARATE; POLYHYDROXYSTEARIC ACID (2300 MW); STEARIC ACID; PROPYLENE CARBONATE; ISODODECANE; TRIMETHYLSILOXYSILICATE (M/Q 0.66); CYCLOMETHICONE 5; GLYCERYL MONOSTEARATE; PEG-10 DIMETHICONE (600 CST); TALC; DIMETHICONE; TROLAMINE; SYNTHETIC WAX (1900 MW); PHENOXYETHANOL; METHYLPARABEN; ETHYLPARABEN; PROPYLPARABEN; BUTYLPARABEN; PROPYLENE GLYCOL; DIAZOLIDINYL UREA; IODOPROPYNYL BUTYLCARBAMATE; PANTHENOL; SODIUM CHLORIDE; .ALPHA.-TOCOPHEROL ACETATE; EDETATE TRISODIUM; TRIETHOXYCAPRYLYLSILANE; TITANIUM DIOXIDE; FERRIC OXIDE RED; FERRIC OXIDE YELLOW; FERROSOFERRIC OXIDE

Always Color Stay-On Makeup SPF 10

ACTIVE INGREDIENT

Sunscreen Active Ingredient (SPF 10): Titanium Dioxide, Octinoxate/Ethylhexyl Methoxycinnamate

PURPOSE

Uses: sunscreen

Keep out of reach of children

INDICATIONS AND USAGE

Discontinue use if signs of irritation occur.

WARNINGS

Caution: For external use only. Avoid contact with eyes. Clinically, Allergy, and irritancy tested. Dermatologist tested.

DOSAGE AND ADMINISTRATION

To use: Shake well. Smooth on with fingers or sponge.

INACTIVE INGREDIENT

Other ingredients:

Water/Aqua, Cyclomethicone, C12-15 Alkyl Benzoate, Alumina, Aluminum Stearate, Polyhydroxystearic Acid, Stearic Acid, Disteardimonium Hectorite, Propylene Glycol, Diazolidnyl Urea, Iodopropynyl Butylcarbamate, Silica Silylate, Stearoyl Inulin, Panthenol, Sodium Chloride, Tocopheryl Acetate, Trisodium EDTA, Triethoxycaprylysilane.

May Contain /+/-: Titanium Dioxide/CI 77891, Iron Oxides/CI 77491/77492/77499.

PACKAGE LABEL

Jafra

Always Color Stay-On

Maquillaje Facial de Larga

Duracion FPS 10

30 ml 1 Fl Oz (US)